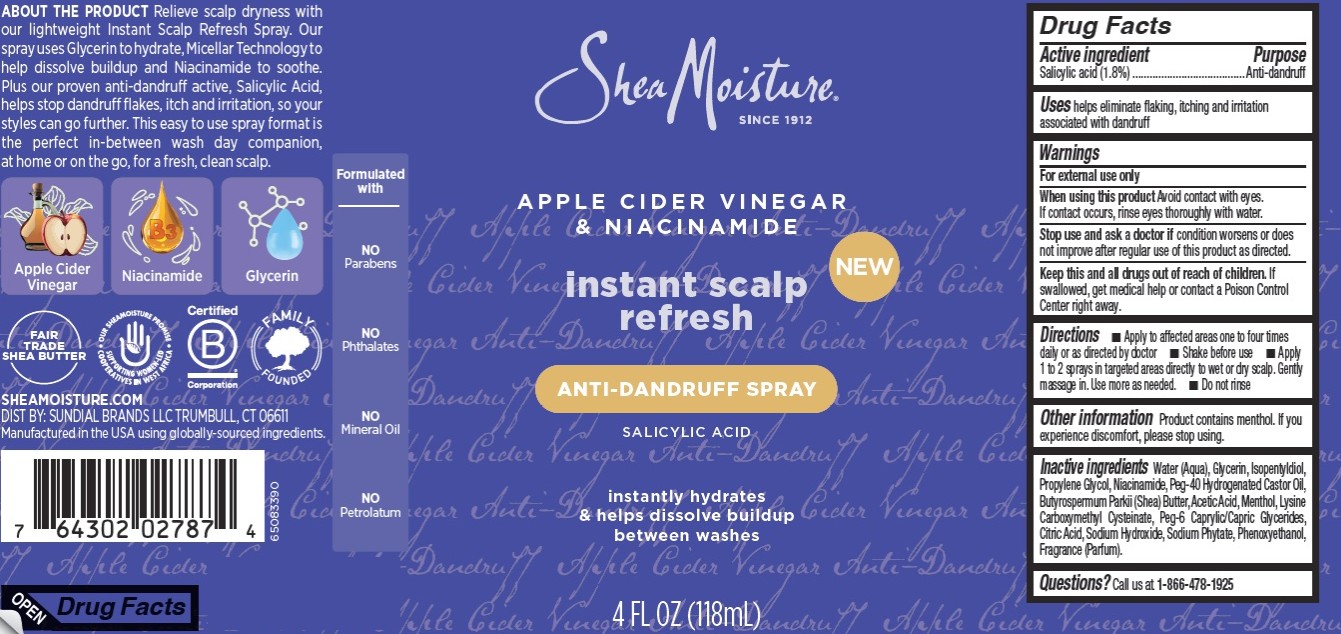 DRUG LABEL: Shea Moisture
NDC: 64942-2390 | Form: LIQUID
Manufacturer: Conopco, Inc. d/b/a Unilever
Category: otc | Type: HUMAN OTC DRUG LABEL
Date: 20251016

ACTIVE INGREDIENTS: SALICYLIC ACID 1.8 g/100 mL
INACTIVE INGREDIENTS: SODIUM HYDROXIDE; GLYCERIN; PROPYLENE GLYCOL; PEG-40 HYDROGENATED CASTOR OIL; PEG-6 CAPRYLIC/CAPRIC GLYCERIDES; SODIUM PHYTATE; CITRIC ACID; PHENOXYETHANOL; ISOPENTYLDIOL; ACETIC ACID; LYSINE CARBOXYMETHYL CYSTEINATE; NIACINAMIDE; BUTYROSPERMUM PARKII (SHEA) BUTTER; WATER; MENTHOL

Shea Moisture Apple Cider Vinegar Instant Scalp Refresh Anti-Dandruff Spray

DESCRIPTION

Shea Moisture Apple Cider Vinegar Instant Scalp Refresh Anti-Dandruff Spray

ACTIVE INGREDIENT

Salicylic acid (1.8%)

PURPOSE

Anti-dandruff

INDICATIONS AND USAGE

helps eliminate flaking, itching and irritation associated with dandruff

WARNINGS

For external use only. When using this product avoid contact with eyes.
If contact occurs, rinse eyes thoroughly with water. Stop use and ask a doctor if condition worsens or does
not improve after regular use of this product as directed.

KEEP OUT OF REACH OF CHILDREN

Keep this and all drugs out of reach of children. If
swallowed, get medical help or contact a Poison Control Center right away.

DOSAGE AND ADMINISTRATION

■ Apply to affected areas one to four times
daily or as directed by doctor ■ Shake before use ■ Apply
1 to 2 sprays in targeted areas directly to wet or dry scalp. Gently
massage in. Use more as needed. ■ Do not rinse

Other information Product contains menthol. If you experience discomfort, please stop using.

INACTIVE INGREDIENT

Water (Aqua), Glycerin, Isopentyldiol, Propylene Glycol, Niacinamide, Peg-40 Hydrogenated Castor Oil, Butyrospermum Parkii (Shea) Butter,Acetic Acid,Menthol, Lysine Carboxymethyl Cysteinate, Peg-6 Caprylic/Capric Glycerides, Citric Acid, Sodium Hydroxide, Sodium Phytate, Phenoxyethanol, Fragrance (Parfum)

QUESTIONS

Call us at 1-866-478-1925